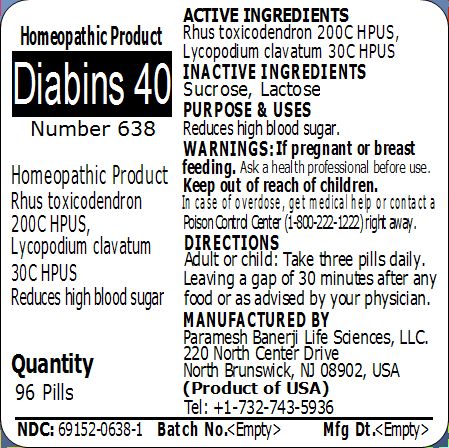 DRUG LABEL: Diabins 40 Number 638
NDC: 69152-0638 | Form: PELLET
Manufacturer: Paramesh Banerji Life Sciences LLC
Category: homeopathic | Type: HUMAN OTC DRUG LABEL
Date: 20150325

ACTIVE INGREDIENTS: TOXICODENDRON PUBESCENS LEAF 200 [hp_C]/1 1; LYCOPODIUM CLAVATUM SPORE 30 [hp_C]/1 1
INACTIVE INGREDIENTS: SUCROSE; LACTOSE

Active Ingredients

Rhus toxicodendron 200C HPUS, Lycopodium clavatum 30C HPUS

Inactive Ingredients

Sucrose, Lactose

Purpose

Reduces high blood sugar

Uses

Reduces high blood sugar

Warnings

If pregnant or breast feeding ask a health professional before use.

Keep out of reach of children. In case of overdose, get medical help or contact a Poison Control Center (1-800-222-1222) right away.

Direction

Adult or child: Take three pills daily. Leaving a gap of 30 minutes after any food or as advised by your physician.

Manufactured by

Paramesh Banerji Life Sciences, LLC

220 North Center Drive

North Brunswick, NJ 08902, USA

Product of USA

Tel: +1-732-743-5936

Principal Display Panel

Homeopathic Product

Diabins 40

Number 638

Homeopathic Product

Rhus toxicodendron 200C HPUS, Lycopodium clavatum 30C HPUS

Reduces high blood sugar

Quantity

96 Pills